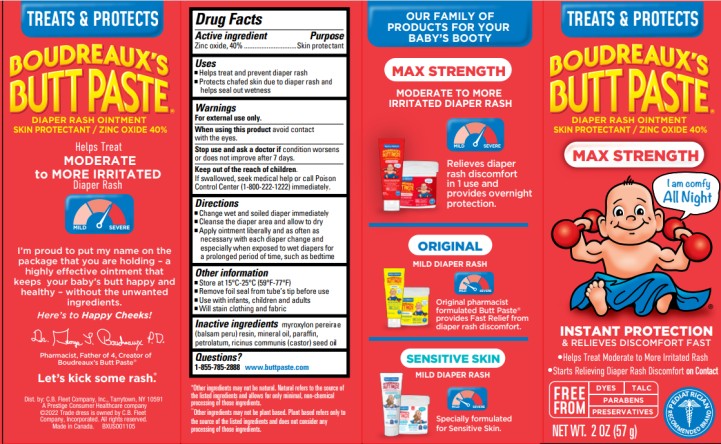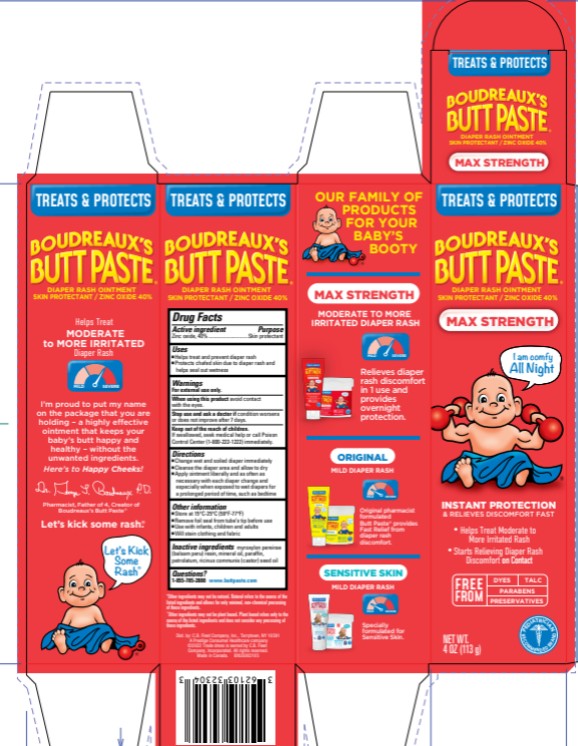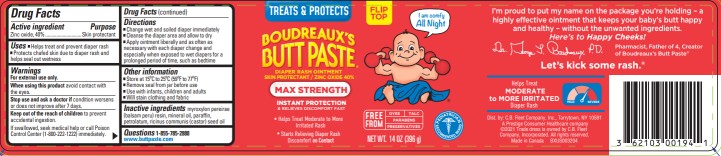 DRUG LABEL: Boudreauxs
NDC: 0132-0323 | Form: CREAM
Manufacturer: C.B. Fleet Company, Inc.
Category: otc | Type: HUMAN OTC DRUG LABEL
Date: 20251030

ACTIVE INGREDIENTS: ZINC OXIDE 40 g/113 g
INACTIVE INGREDIENTS: BALSAM PERU; MINERAL OIL; PARAFFIN; PETROLATUM; CASTOR OIL

Boudreauxs Complete Rash Kit - Max 2BP_0132-0323

Drug Facts

Active Ingredient

Zinc Oxide, 40%

Purpose

Skin Protectant

Uses

- Helps treat and prevent diaper rash
- Protects chafed skin due to diaper rash and helps seal out wetness

Warnings

- For external use only
- When using this product avoid contact with the eyes

Stop use and ask a doctor if

condition worsens or does not improve after 7 days

Keep out of reach of children

If swallowed, seek medical help or call Poison Control Center (1-800-222-1222) immediately

Directions

- Change wet and soiled diaper immediately
- Cleanse the diaper area and allow to dry
- Apply ointment liberally and as often as necessary with each diaper change and especially when exposed to wet diapers for a prolonged period of time, such as bedtime

Other Information

- Store at room temperature, 15C to 25 C (59F to 77F)
- Remove foil seal from the tube's tip
- Use with infants, children and adults
- Will stain clothing and fabric

Inactive Ingredients

myroxylon pereirae (balsam peru) resin, mineral oil, paraffin, petrolatum, ricinus communis (castor) seed oil

Questions?

1-855-785-2888 www.buttpaste.com

PRINCIPAL DISPLAY PANEL

TREATS & PROTECTS
BOUDREAUX’S
BUTT PASTE
MAX STRENGTH
NET WT. 2 OZ (57 g)

PRINCIPAL DISPLAY PANEL

BOUDREAUX’S
BUTT PASTE
Zinc oxide 40%
MAX STRENGTH
NET WT. 4 OZ (113 g)

PRINCIPAL DISPLAY PANEL

BOUDREAUX’S
BUTT PASTE
Zinc oxide 40%
MAX STRENGTH
NET WT. 14 OZ (396 g)